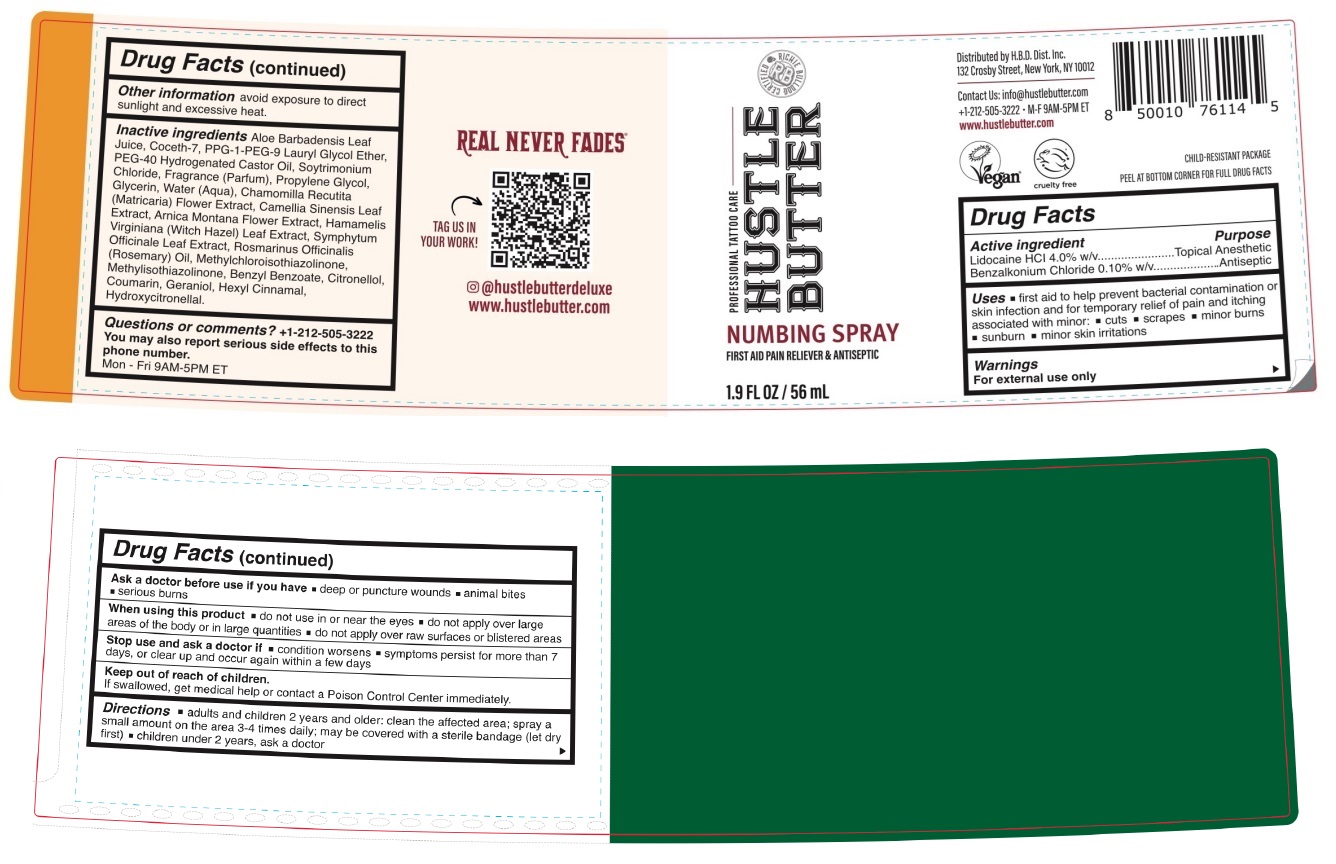 DRUG LABEL: HUSTLE BUTTER NUMBING
NDC: 72014-300 | Form: SPRAY
Manufacturer: H.B.D. DIST. INC.
Category: otc | Type: HUMAN OTC DRUG LABEL
Date: 20250110

ACTIVE INGREDIENTS: LIDOCAINE HYDROCHLORIDE 4 g/100 mL; BENZALKONIUM CHLORIDE 0.10 g/100 mL
INACTIVE INGREDIENTS: ALOE VERA LEAF; COCETH-7; PPG-1-PEG-9 LAURYL GLYCOL ETHER; POLYOXYL 40 HYDROGENATED CASTOR OIL; TRIMETHYLAMINE HYDROCHLORIDE; PROPYLENE GLYCOL; GLYCERIN; WATER; CHAMOMILE; GREEN TEA LEAF; ARNICA MONTANA FLOWER; HAMAMELIS VIRGINIANA LEAF; COMFREY LEAF; ROSEMARY OIL; METHYLCHLOROISOTHIAZOLINONE; METHYLISOTHIAZOLINONE; BENZYL BENZOATE; .BETA.-CITRONELLOL, (R)-; COUMARIN; GERANIOL; .ALPHA.-HEXYLCINNAMALDEHYDE; HYDROXYCITRONELLAL

HUSTLE BUTTER NUMBING SPRAY

Active ingredient

Lidocaine HCl 4.0% w/v
Benzalkonium Chloride 0.10% w/v

Purpose

Topical Anesthetic
Antiseptic

Uses

• first aid to help prevent bacterial contamination or skin infection and for temporary relief of pain and itching associated with minor: • cuts • scrapes • minor burns • sunburn • minor skin irritations

Warnings

For external use only

Ask a doctor before use if you have • deep or puncture wounds • animal bites • serious burns

When using this product • do not use in or near the eyes • do not apply over large areas of the body or in large quantities • do not apply over raw surfaces or blistered areas

Stop use and ask a doctor if • condition worsens • symptoms persist for more than 7 days, or clear up and occur again within a few days

Keep out of reach of children.
If swallowed, get medical help or contact a Poison Control Center immediately.

Directions

• adults and children 2 years and older: clean the affected area; spray a small amount on the area 3-4 times daily; may be covered with a sterile bandage (let dry first) • children under 2 years, ask a doctor

Other information

avoid exposure to direct sunlight and excessive heat.

Inactive ingredients

Aloe Barbadensis Leaf Juice, Coceth-7, PPG-1-PEG-9 Lauryl Glycol Ether, PEG-40 Hydrogenated Castor Oil, Soytrimonium Chloride, Fragrance (Parfum), Propylene Glycol, Glycerin, Water (Aqua), Chamomilla Recutita (Matricaria) Flower Extract, Camellia Sinensis Leaf Extract, Arnica Montana Flower Extract, Hamamelis Virginiana (Witch Hazel) Leaf Extract, Symphytum Officinale Leaf Extract, Rosmarinus Officinalis (Rosemary) Oil, Methylchloroisothiazolinone, Methylisothiazolinone, Benzyl Benzoate, Citronellol, Coumarin, Geraniol, Hexyl Cinnamal, Hydroxycitronellal.

Questions or comments?

+1-212-505-3222
You may also report serious side effects to this phone number.
Mon - Fri 9AM-5PM ET

PROFESSIONAL TATTOO CARE

FIRST AID PAIN RELIEVER & ANTISEPTIC

Distributed by H.B.D. Dist. Inc.
132 Crosby Street, New York, NY 10012

Contact Us: info@hustlebutter.com
www.hustlebutter.com

Vegan

cruelty free

CHILD-RESISTANT PACKAGE

PEEL AT BOTTOM CORNER FOR FULL DRUG FACTS

REAL NEVER FADES

@hustlebutterdeluxe
www.hustlebutter.com